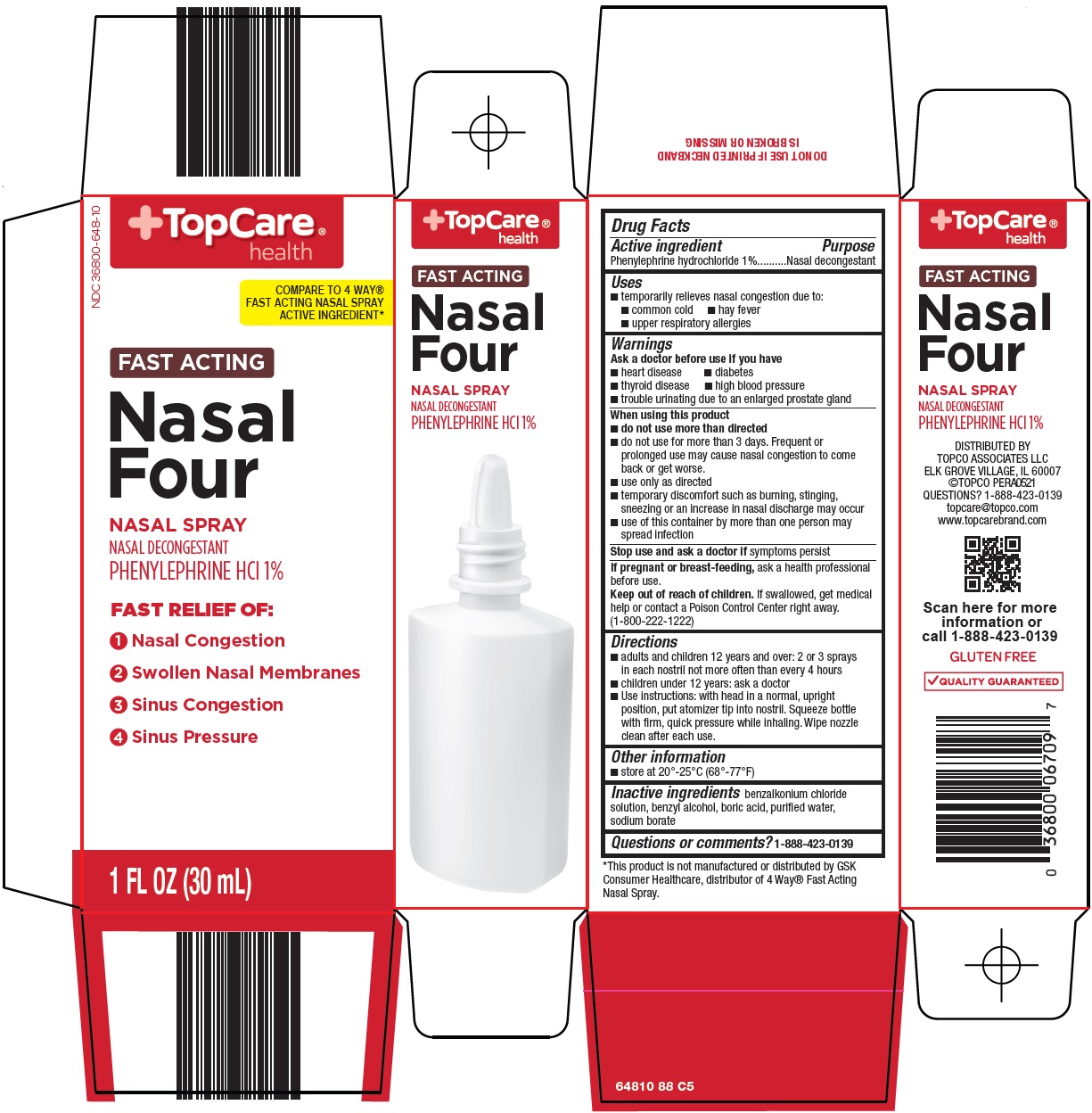 DRUG LABEL: Topcare Nasal Four
NDC: 36800-648 | Form: SPRAY
Manufacturer: Topco Associates LLC
Category: otc | Type: HUMAN OTC DRUG LABEL
Date: 20241004

ACTIVE INGREDIENTS: PHENYLEPHRINE HYDROCHLORIDE 1 g/100 mL
INACTIVE INGREDIENTS: BENZALKONIUM CHLORIDE; BENZYL ALCOHOL; BORIC ACID; SODIUM BORATE; WATER

Topco Associates LLC. Nasal Four Drug Facts

Active ingredient

Phenylephrine hydrochloride 1%

Purpose

Nasal decongestant

Uses

1. temporarily relieves nasal congestion due to:
2. common cold
3. hay fever
4. upper respiratory allergies

Warnings

Ask a doctor before use if you have

1. heart disease
2. diabetes
3. thyroid disease
4. high blood pressure
5. trouble urinating due to an enlarged prostate gland

When using this product

1. do not use more than directed
2. do not use for more than 3 days. Frequent or prolonged use may cause nasal congestion to come back or get worse.
3. use only as directed
4. temporary discomfort such as burning, stinging, sneezing or an increase in nasal discharge may occur
5. use of this container by more than one person may spread infection

Stop use and ask a doctor if

symptoms persist

If pregnant or breast-feeding,

ask a health professional before use.

Keep out of reach of children.

If swallowed, get medical help or contact a Poison Control Center right away. (1-800-222-1222)

Directions

1. adults and children 12 years and over: 2 or 3 sprays in each nostril not more often than every 4 hours
2. children under 12 years: ask a doctor
3. Use instructions: with head in a normal, upright position, put atomizer tip into nostril. Squeeze bottle with firm, quick pressure while inhaling. Wipe nozzle clean after each use.

Other information

1. store at 20°-25°C (68°-77°F)

Inactive ingredients

benzalkonium chloride, benzyl alcohol, boric acid, purified water, sodium borate

Questions or comments?

1-888-423-0139

Principal Display Panel

TopCare® health

COMPARE TO 4-WAY® FAST ACTING NASAL SPRAY ACTIVE INGREDIENT

FAST ACTING

Nasal Four

NASAL SPRAY

NASAL DECONGESTANT

PHENYLEPHRINE HCl 1%

FAST RELIEF OF:

1 Nasal Congestion

2 Swollen Nasal Membranes

3 Sinus Congestion

4 Sinus Pressure

1 FL OZ (30 mL)